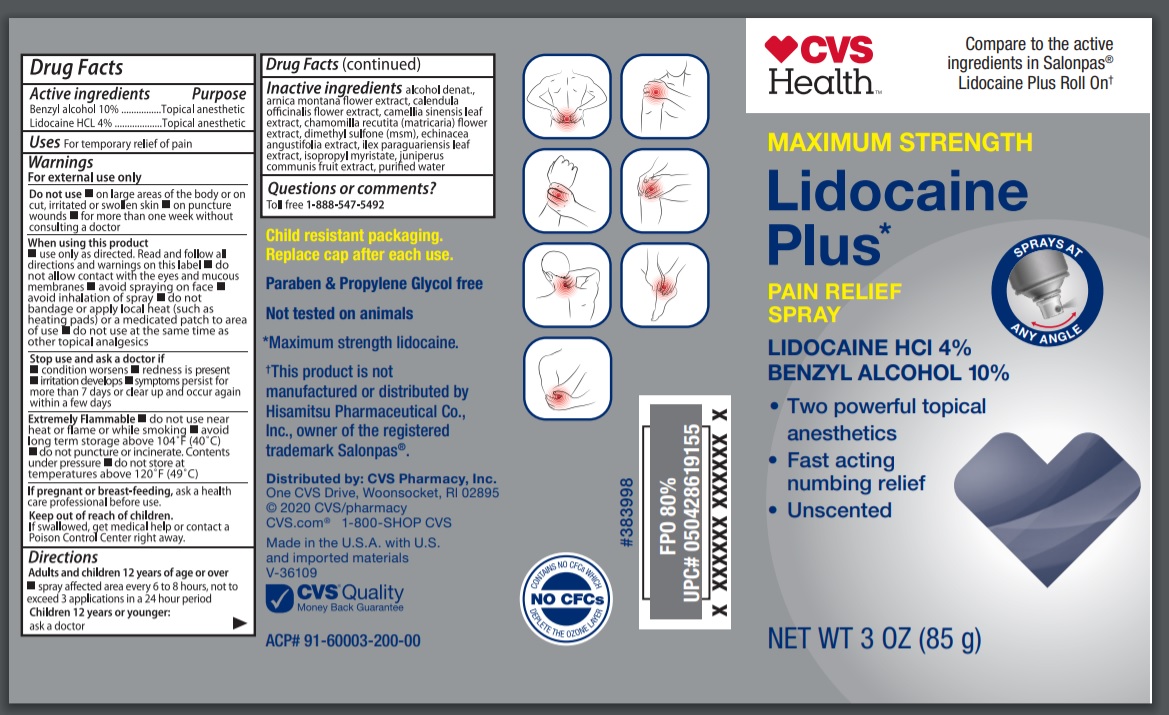 DRUG LABEL: CVS Maximum Strength LIDOCAINE PLUS
NDC: 69842-573 | Form: SPRAY
Manufacturer: CVS Pharmacy Inc.
Category: otc | Type: HUMAN OTC DRUG LABEL
Date: 20231126

ACTIVE INGREDIENTS: BENZYL ALCOHOL 10 g/100 g; LIDOCAINE HYDROCHLORIDE 4 g/100 g
INACTIVE INGREDIENTS: ALCOHOL; ARNICA MONTANA FLOWER; CALENDULA OFFICINALIS FLOWER; GREEN TEA LEAF; CHAMOMILE; DIMETHYL SULFONE; ECHINACEA ANGUSTIFOLIA WHOLE; ILEX PARAGUARIENSIS LEAF; ISOPROPYL MYRISTATE; JUNIPER BERRY; WATER

CVS Health Lidocaine Plus

Active ingredients

Benzyl alcohol 10%

Lidocaine HCl 4%

Purpose

Topical anesthetic

Uses

For temporary relief of pain

Warnings

For external use only

Flammable:

Keep away from fire or flame

-Do not use near heat or flame or while smoking.

-avoid long term storage above 40 degree Celcius.

-do not puncture or incinerate. COntents under pressure

-do not store at temperatures above 49 degree Celcius

Do not use

- on large areas of the body or cut or wounds or damaged skin
- on puncture wounds
- for more than one week without consulting a doctor

When using this product

- use only as directed
- avoid contact with the eyes, mucous membranes or rashes
- avoid spraying on face
- avoid inhalation of spray
- do not bandage or apply local heat such as heating pads or a medicated patch to area of use
- do not use at the same time as other topical analgesics

Stop use and ask a doctor if

- skin reactions occur, such as rash, itching, redness, irritaion, pain, swelling and blistering
- conditions worsen
- symptoms persist for more than 7 days
- symptoms clear up and occur again within a few days

If pregnant or breast-feeding,

ask a health professional before use.

Keep out of reach of children.

If swallowed, get medical help or contact a Poison Control Center right away.

Directions

Adults and children 12 years of age and over:

- spray to affected area not more than 3 to 4 times daily

Children under 12 years of age:

consult a doctor

Other information

- Avoid storing product in direct sunlight
- Protect product from excessive moisture
- Store with lid closed tighly

Inactive ingredients

alcohol denatured, arnica montana flower extract, calendula officinalis flower extract, camellia sinensis leaf extract, chamomilla recutita (matricaria) flower extract , dimethyl sulfone (msm), Echinacea angustifolia extract, ilex paraguariensis leaf extract, isopropyl myristate, juniperus communis fruit extract, purified water

Questions or comments?

Toll free 1-888-547-5492